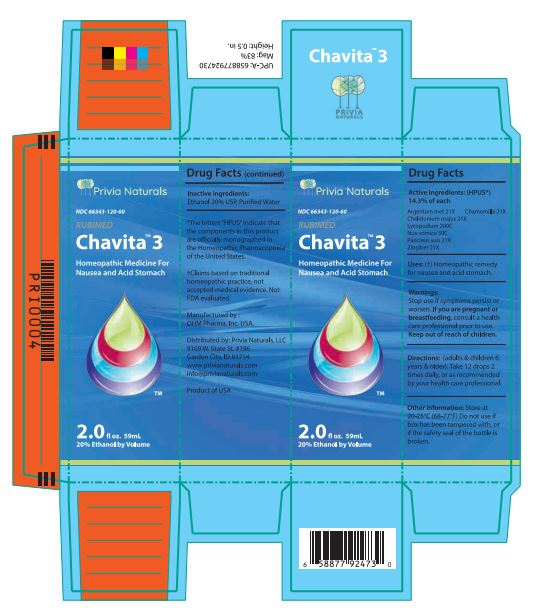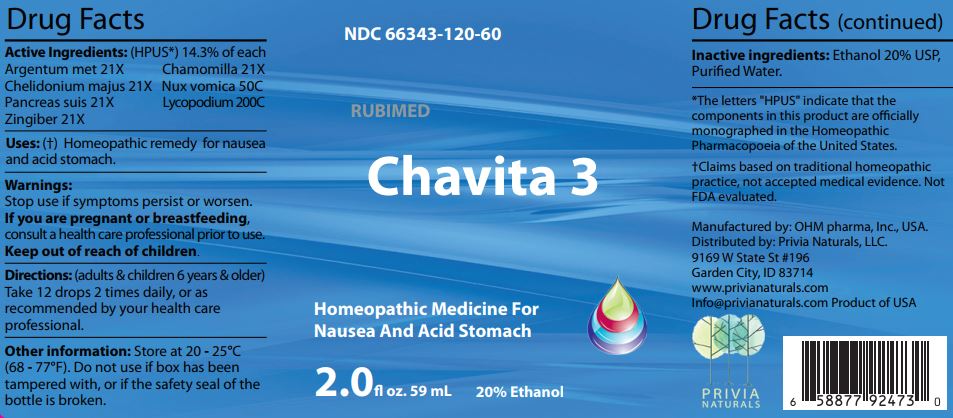 DRUG LABEL: Chavita 3
NDC: 66343-120 | Form: LIQUID
Manufacturer: RUBIMED AG
Category: homeopathic | Type: HUMAN OTC DRUG LABEL
Date: 20241029

ACTIVE INGREDIENTS: SILVER 21 [hp_X]/60 mL; MATRICARIA CHAMOMILLA WHOLE 21 [hp_X]/60 mL; CHELIDONIUM MAJUS WHOLE 21 [hp_X]/60 mL; STRYCHNOS NUX-VOMICA SEED 50 [kp_C]/60 mL; SUS SCROFA PANCREAS 21 [hp_X]/60 mL; LYCOPODIUM CLAVATUM SPORE 200 [hp_C]/60 mL; GINGER 21 [hp_X]/60 mL
INACTIVE INGREDIENTS: ALCOHOL; WATER

Chavita 3

ACTIVE INGREDIENT

Drug Facts Active Ingredients: (HPUS*) 14.3% of each

Argentum met 21X Chamomilla 21X

Chelidonium majus 21X Nux vomica 50C

Pancreas suis 21X Lycopodium 200C

Zingiber 21X

*The letters "HPUS" indicate that the components in this product are officially monographed in the Homeopathic Pharmacopoeia of the United States. †Claims based on traditional homeopathic practice, not accepted medical evidence. Not FDA evaluated.

INDICATIONS AND USAGE

Uses: (†) Homeopathic remedy for nausea and acid stomach.

Warnings:

Stop use if symptoms persist or worsen.

If you are pregnant or breastfeeding,consult a healthcare professional prior to use.

Keep out of reach of children.

DOSAGE AND ADMINISTRATION

Directions: (adults & children 6 years & older)

Take 12 drops 2 times daily, or as recommended by your health care professional.

Other information: Store at 20 - 25°C

(68 - 77°F.) Do not use if box has been

tampered with, or if the safety seal of the

bottle is broken.

Inactive ingredients:Ethanol 20% USP,

Purified Water.

QUESTIONS

Manufactured by: OHM pharma, Inc, USA.

Distributed by: Privia Naturals, LLC.

9169 W State St #196

Garden City, ID 83714

www.privianaturals.com

Info@privianaturals.com Product of USA.

PACKAGE LABEL

NDC 66343-120-60

RUBIMED

Chavita 3

Homeopathic Medicine For

Nausea And Stomach Acid

2.0 fl oz. 59mL 20% Ethanol

PURPOSE

Homeopathic Medicine For

Nausea And Acid Stomach